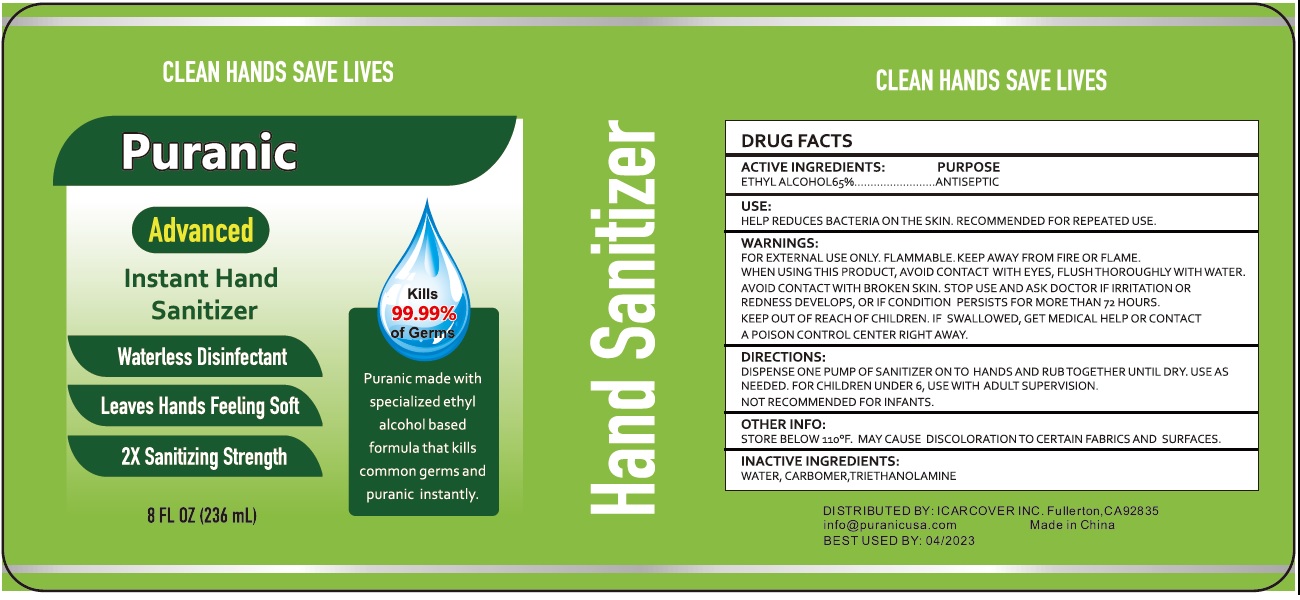 DRUG LABEL: Instant Hand Sanitizer
NDC: 75248-000 | Form: GEL
Manufacturer: ICARCOVER INC.
Category: otc | Type: HUMAN OTC DRUG LABEL
Date: 20231025

ACTIVE INGREDIENTS: ALCOHOL 0.65 mL/1 mL
INACTIVE INGREDIENTS: WATER; CARBOMER HOMOPOLYMER, UNSPECIFIED TYPE; TROLAMINE

Instant Hand Sanitizer

ACTIVE INGREDIENTS:

ETHYL ALCOHOL 65%

PURPOSE

ANTISEPTIC

USE:

HELP REDUCES BACTERIA ON THE SKIN. RECOMMENDED FOR REPEATED USE.

WARNINGS

FOR EXTERNAL USE ONLY. FLAMMABLE. KEEP AWAY FROM FIRE OR FLAME.

WHEN USING THIS PRODUCT

AVOID CONTACT WITH EYES, FLUSH THOROUGHLY WITH WATER. AVOID CONTACT WITH BROKEN SKIN.

STOP USE AND ASK DOCTOR IF IRRITATION OR REDNESS DEVELOPS, OR IF CONDITION PERSISTS FOR MORE THAN 72 HOURS.

KEEP OUT OF REACH OF CHILDREN.

IF SWALLOWED, GET MEDICAL HELP OR CONTACT A POISON CONTROL CENTER RIGHT AWAY.

DIRECTIONS

DISPENSE ONE PUMP OF SANITIZER ONTO HANDS AND RUB TOGETHER UNTIL DRY. USE AS NEEDED. FOR CHILDREN UNDER 6, USE WITH ADULT SUPERVISION. NOT RECOMMENDED FOR INFANTS.

OTHER INFO:

STORE BELOW 110°F. MAY CAUSE DISCOLORATION TO CERTAIN FABRICS AND SURFACES.

INACTIVE INGREDIENTS:

WATER, CARBOMER, TRIETHANOLAMINE